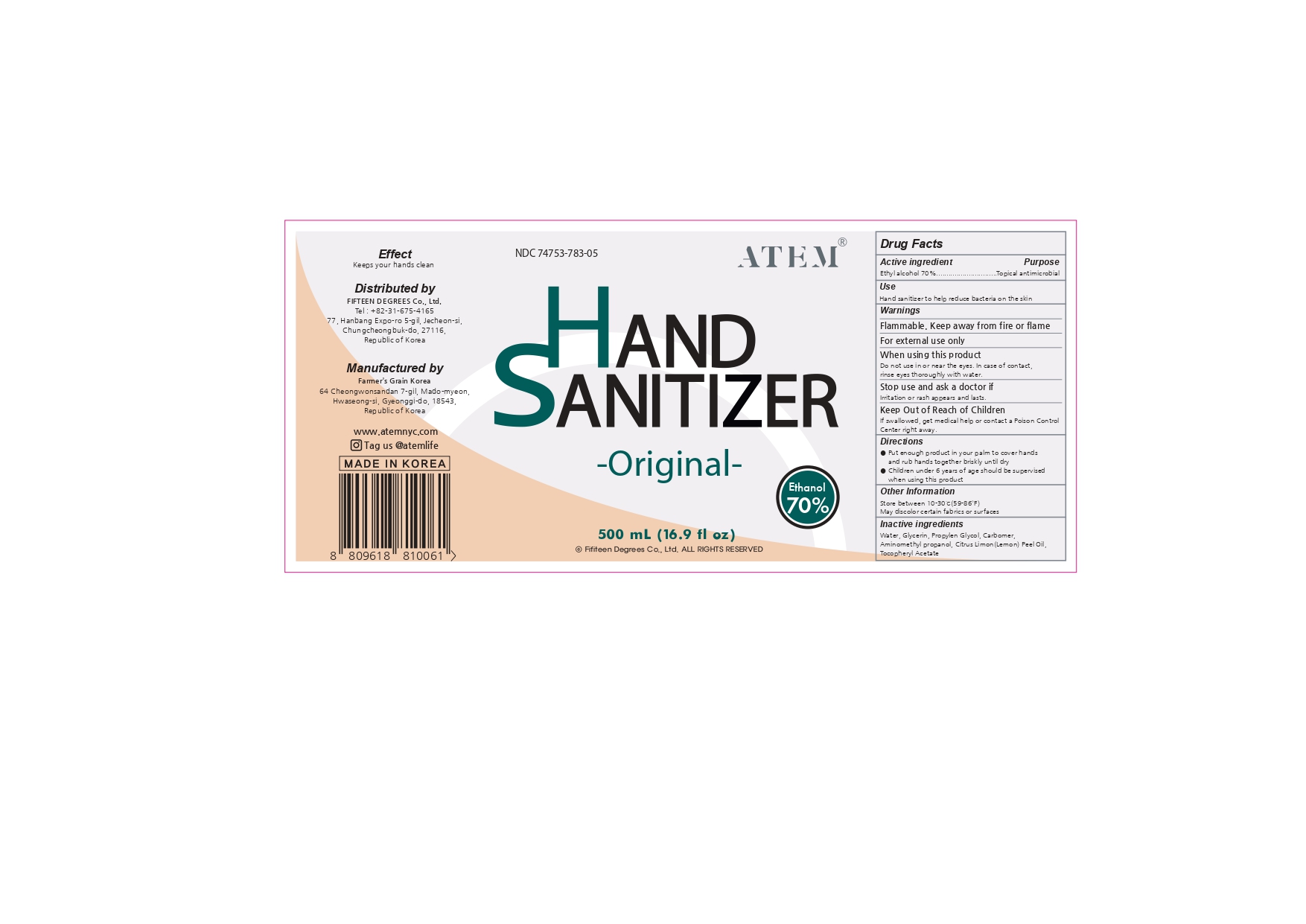 DRUG LABEL: Hand Sanitizer
NDC: 74753-783 | Form: LIQUID
Manufacturer: FIFTEEN DEGREES co.,ltd
Category: otc | Type: HUMAN OTC DRUG LABEL
Date: 20210109

ACTIVE INGREDIENTS: ALCOHOL 70 mL/70 mL
INACTIVE INGREDIENTS: CARBOMER HOMOPOLYMER, UNSPECIFIED TYPE; AMINOMETHYLPROPANOL; PROPYLENE GLYCOL; GLYCERIN; .ALPHA.-TOCOPHEROL ACETATE, D-; WATER; LEMON OIL

Hand Sanitizer Fifteen Degrees

ACTIVE INGREDIENT

Ethyl Alcohol 70%

Warnings
Flammable. Keep away from fire or flame

For external use only

When using this product Do not use in or near the eyes. In case of contact,rinse eyes thoroughly with water.

Stop use and ask a doctor if irritation or rash appears and lasts.

Keep Out of Reach of Children
If swallowed, get medical help or contact a Poison Control

Center right away.

Directions

● Put enough product in your palm to cover hands and rub hands together briskly until dry

● Children under 6 years of age should be supervised when using this product

Inactive ingredients

Water, Glycerin, Propylen Glycol, Carbomer,
Aminomethyl propanol, Citrus Limon(Lemon) Peel Oil,
Tocopheryl Acetate

Keep Out of Reach of Children
If swallowed, get medical help or contact a Poison Control Center right away.

INDICATIONS AND USAGE

Use: Hand sanitizer to help reduce bacteria on the skin

purpose topical antimicrobial

PACKAGE LABEL

NDC 74753-783-05

ATEM

Hand cleaner

sanitizer

ethanol 70%

500 mL (16.9 fl oz)